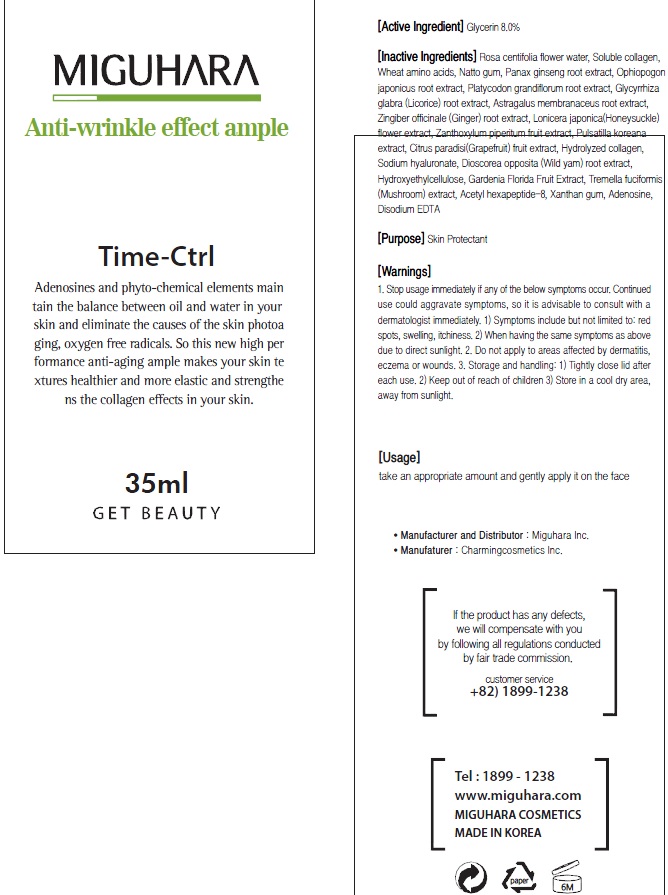 DRUG LABEL: Anti Wrinkle Effect Ample
NDC: 70380-090 | Form: SOLUTION
Manufacturer: MIGUHARA
Category: otc | Type: HUMAN OTC DRUG LABEL
Date: 20160218

ACTIVE INGREDIENTS: Glycerin 2.8 g/35 mL
INACTIVE INGREDIENTS: ROSA CENTIFOLIA FLOWER; Water

ACTIVE INGREDIENT

Active Ingredient: Glycerin 8.0%

INACTIVE INGREDIENT

Inactive Ingredients: Rosa centifolia flower, Water, Soluble collagen, Wheat amino acids, Natto gum, Panax ginseng root extract, Ophiopogon japonicus root extract, Platycodon grandiflorum root extract, Glycyrrhiza glabra (Licorice) root extract, Astragalus membranaceus root extract, Zingiber officinale (Ginger) root extract, Lonicera japonica(Honeysuckle) flower extract, Zanthoxylum piperitum fruit extract, Pulsatilla koreana extract, Citrus paradisi(Grapefruit) fruit extract, Hydrolyzed collagen, Sodium hyaluronate, Dioscorea opposita (Wild yam) root extract, Hydroxyethylcellulose, Gardenia Florida Fruit Extract, Tremella fuciformis (Mushroom) extract, Acetyl hexapeptide-8, Xanthan gum, Adenosine, Disodium EDTA

PURPOSE

Purpose: Skin Protectant

WARNINGS

1. Stop usage immediately if any of the below symptoms occur. Continued use could aggravate symptoms, so it is advisable to consult with a dermatologist immediately. 1) Symptoms include but not limited to: red spots, swelling, itchiness. 2) When having the same symptoms as above due to direct sunlight. 2. Do not apply to areas affected by dermatitis, eczema or wounds. 3. Storage and handling: 1) Tightly close lid after each use. 2 Keep out of reach of children 3) Store in a cool dry area, away from sunlight

KEEP OUT OF REACH OF CHILDREN

Usage

Usage: Take an appropriate amount and gently apply it on the face.

Usage

Usage: Take an appropriate amount and gently apply it on the face.